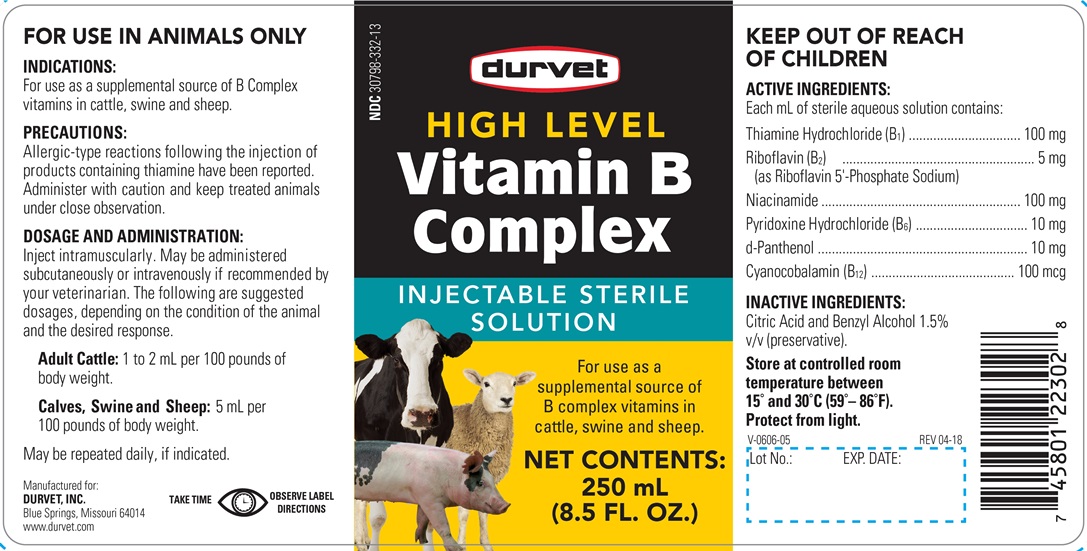 DRUG LABEL: HIGH LEVEL VITAMIN B COMPLEX
NDC: 30798-332 | Form: INJECTION
Manufacturer: Durvet, Inc.
Category: animal | Type: OTC ANIMAL DRUG LABEL
Date: 20250227

ACTIVE INGREDIENTS: CYANOCOBALAMIN 0.1 mg/1 mL; THIAMINE HYDROCHLORIDE 100 mg/1 mL; PYRIDOXINE HYDROCHLORIDE 10 mg/1 mL; NIACINAMIDE 100 mg/1 mL; DEXPANTHENOL 10 mg/1 mL; RIBOFLAVIN 5'-PHOSPHATE SODIUM 5 mg/1 mL
INACTIVE INGREDIENTS: BENZYL ALCOHOL; CITRIC ACID MONOHYDRATE

High Level Vitamin B Complex

INDICATIONS AND USAGE

FOR ANIMAL USE ONLY

KEEP OUT OF REACH OF CHILDREN

Injectable Sterile Solution

Indications

For use as a supplemental source of B complex vitamins in cattle, swine and sheep.

PRECAUTIONS

Allergic-type reactions following the injection of products containing thiamine have been reported. Administer with caution and keep treated animals under close observation.

DOSAGE AND ADMINISTRATION

Inject intramuscularly. May be administered subcutaneously or intravenously if recommended by your veterinarian. The following are suggested dosages, depending on the condition of the animal and the desired response.

Adult Cattle- 1 to 2 mL per 100 pounds of body weight.

Calves, Swine and Sheep- 5 mL per 100 pounds of body weight.

Maybe repeated daily, if indicated.

TAKE TIME OBSERVE LABEL DIRECTIONS

COMPONENTS

Each mL of sterile aqueous solution contains:

ACTIVE INGREDIENTS

Thiamine Hydrochloride (B1) 100 mg, Riboflavin (B2) (as Riboflavin 5'-Phosphate Sodium) 5 mg, Niacinamide 100 mg, Pyridoxine Hydrochloride (B6) 10 mg, d-Panthenol , Cyanocobalamin (B12) 100 mcg

INACTIVE INGREDIENTS

Citric Acid and Benzyl Alcohol 1.5% v/v (preservative).

STORAGE AND HANDLING

Store at controlled room temperature between 15° and 30°C (59°-86°F)

Protect from light.